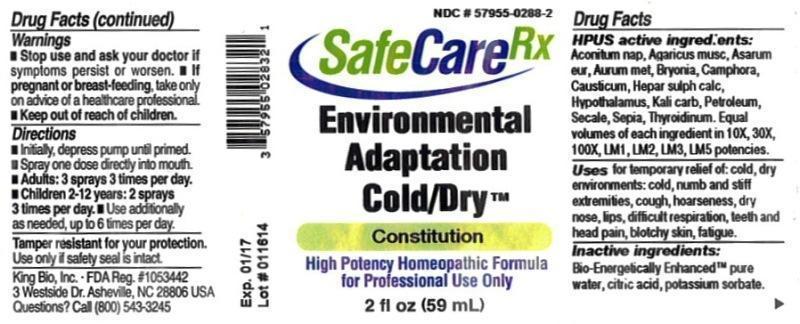 DRUG LABEL: Environmental Adaptation Cold and Dry
NDC: 57955-0288 | Form: LIQUID
Manufacturer: King Bio Inc.
Category: homeopathic | Type: HUMAN OTC DRUG LABEL
Date: 20140417

ACTIVE INGREDIENTS: ACONITUM NAPELLUS 10 [hp_X]/59 mL; AMANITA MUSCARIA FRUITING BODY 10 [hp_X]/59 mL; ASARUM EUROPAEUM 10 [hp_X]/59 mL; GOLD 10 [hp_X]/59 mL; BRYONIA ALBA ROOT 10 [hp_X]/59 mL; CAMPHOR (NATURAL) 10 [hp_X]/59 mL; CAUSTICUM 10 [hp_X]/59 mL; CALCIUM SULFIDE 10 [hp_X]/59 mL; BOS TAURUS HYPOTHALAMUS 10 [hp_X]/59 mL; POTASSIUM CARBONATE 10 [hp_X]/59 mL; KEROSENE 10 [hp_X]/59 mL; CLAVICEPS PURPUREA SCLEROTIUM 10 [hp_X]/59 mL; SEPIA OFFICINALIS JUICE 10 [hp_X]/59 mL; THYROID, UNSPECIFIED 10 [hp_X]/59 mL
INACTIVE INGREDIENTS: WATER; CITRIC ACID MONOHYDRATE; POTASSIUM SORBATE

Environmental Adaptation Cold and Dry

Drug Facts

____________________________________________________________________________________________________________________

HPUS active ingredients: Aconitum napellus, Agaricus muscarius, Asarum europaeum, Aurum metallicum, Bryonia, Camphora, Causticum, Hepar sulphuris calcareum, Hypothalamus, Kali carbonicum, Petroleum, Secale cornutum, Sepia, Thyroidinum. Equal volumes of each ingredient in 10X, 30X, 100X, LM1, LM2, LM3, LM5 potencies.

INDICATIONS AND USAGE

Uses for temporary relief of: cold, dry environments: cold, numb and stiff extremities, cough, hoarseness, dry nose, lips, difficult respiration, teeth and head pain, blotchy skin, fatigue.

INACTIVE INGREDIENT

Inactive ingredients: Bio-Energetically Enhanced pure water, citric acid, potassium sorbate.

Warnings

- Stop use and ask your doctor if symptoms persist or worsen.
- If pregnant or breast-feeding, take only on advice of a healthcare professional.

- Keep out of reach of children.

Directions:

- Initially, depress pump until primed.
- Spray one dose directly into mouth.
- Adults: 3 sprays 3 times per day.
- Children 2-12 years: 2 sprays 3 times per day.
- Use additionally as needed, up to 6 times per day.

OTHER SAFETY INFORMATION

Tamper resistant for your protection. Use only if safety seal is intact.

PURPOSE

Uses for temporary relief of: cold, dry environments:

- cold, numb and stiff extremities
- cough
- hoarseness
- dry nose
- lips
- difficult respiration
- teeth and head pain
- blotchy skin
- fatigue